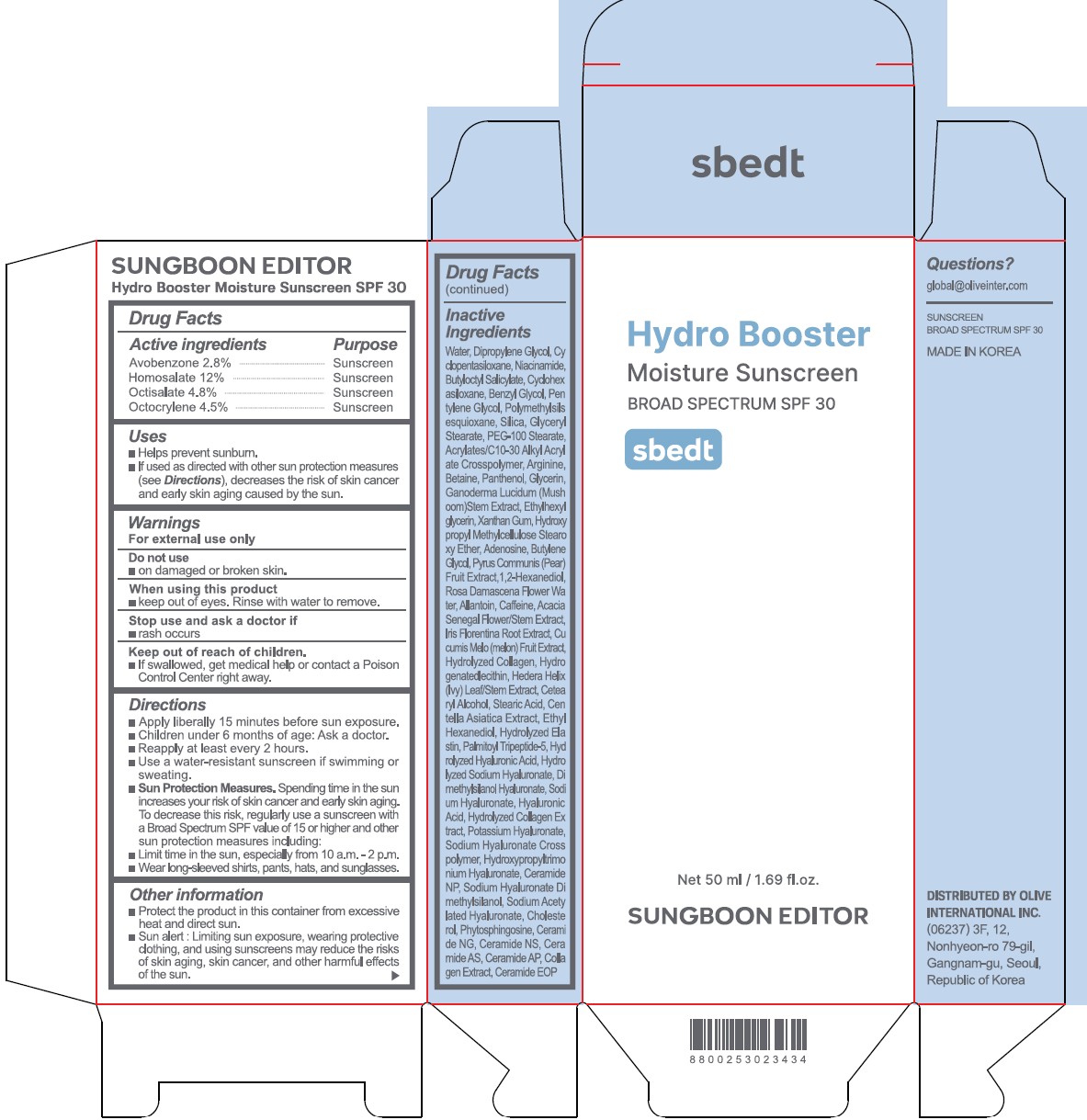 DRUG LABEL: Sungboon Editor Hydro Booster Moisture Sunscreen
NDC: 85037-001 | Form: CREAM
Manufacturer: Olive International Inc.
Category: otc | Type: HUMAN OTC DRUG LABEL
Date: 20250310

ACTIVE INGREDIENTS: HOMOSALATE 120 mg/1 mL; OCTISALATE 48 mg/1 mL; OCTOCRYLENE 45 mg/1 mL; AVOBENZONE 28 mg/1 mL
INACTIVE INGREDIENTS: WATER; DIPROPYLENE GLYCOL; CYCLOMETHICONE 5; NIACINAMIDE; BUTYLOCTYL SALICYLATE; CYCLOMETHICONE 6; ETHYLENE GLYCOL MONOBENZYL ETHER; PENTYLENE GLYCOL; POLYMETHYLSILSESQUIOXANE (4.5 MICRONS); SILICON DIOXIDE; GLYCERYL MONOSTEARATE; PEG-100 MONOSTEARATE; ACRYLATES/C10-30 ALKYL ACRYLATE CROSSPOLYMER (60000 MPA.S AT 0.5%); ARGININE; BETAINE; MAGNESIUM SULFATE, UNSPECIFIED FORM; PANTHENOL; GLYCERIN; GANODERMA LUCIDUM STEM; ETHYLHEXYLGLYCERIN; XANTHAN GUM; HYPROMELLOSE 2208 0.45% STEAROXY ETHER; ADENOSINE; BUTYLENE GLYCOL; PEAR; 1,2-HEXANEDIOL; ROSA X DAMASCENA FLOWER OIL; ALLANTOIN; CAFFEINE; SENEGALIA SENEGAL FLOWER; IRIS X GERMANICA NOTHOVAR. FLORENTINA ROOT; MUSKMELON; HYDROGENATED SOYBEAN LECITHIN; HEDERA HELIX TOP; CETOSTEARYL ALCOHOL; STEARIC ACID; CENTELLA ASIATICA TRITERPENOIDS; ETHOHEXADIOL; HYDROLYZED BOVINE ELASTIN (BASE; 1000 MW); PALMITOYL TRIPEPTIDE-5; DIMETHYLSILANOL HYALURONATE; HYALURONATE SODIUM; HYALURONIC ACID; PEG-9 DIGLYCIDYL ETHER/SODIUM HYALURONATE CROSSPOLYMER; CERAMIDE NP; SODIUM ACETYLATED HYALURONATE; CHOLESTEROL; PHYTOSPHINGOSINE; CERAMIDE NG; CERAMIDE NS; N-BUTYRYL-D-ERYTHRO-SPHINGOSINE; CERAMIDE AP

85037-001_Sungboon Editor Hydro Booster Moisture Sunscreen

ACTIVE INGREDIENT

Avobenzone 2.8%

Homosalate 12%

Octisalate 4.8%

Octocrylene 4.5%

PURPOSE

Sunscreen

INDICATIONS AND USAGE

Helps prevent sunburn
If used as directed with other sun protection measures (see Directions) decrease the risk of skin cancer and early skin aging caused by the sun

DOSAGE AND ADMINISTRATION

Apply liberally 15 minutes before sun exposure

Children under 6 months or age: Ask a doctor.

Reapply at least every two hours
Use a water-resistant sunscreen if swimming or sweating
Sun protection measures. Spending time in the sun increases your risk of skin cancer and early skin aging. To decrease this risk, regularly use a sunscreen with a broad spectrum SPF or 15 of higher and other sun protection measures including:

Limited time in the sun, especially from 10 am to 2 pm.

Wear long-sleeve shirts, pants, hats, and sunglasses

WARNINGS

For external use only

Do not use on damaged or broken skin

When using this product, keep out of eyes. Rinse with water to remove.

Stop use and ask a doctor if rash occurs.

Keep out of reach of the children.

If swallowed, get medical help or contact a poison control center right away.

INACTIVE INGREDIENT

Water, Dipropylene Glycol, Cyclopentasiloxane, Niacinamide, Butyloctyl Salicylate, Cyclohexasiloxane, Benzyl Glycol, Pentylene Glycol, Polymethylsilsesquioxane, Silica, Glyceryl Stearate, PEG-100 Stearate, Acrylates/C10-30 Alkyl Acrylate Crosspolymer, Arginine, Betaine, Panthenol, Glycerin, Ganoderma Lucidum (Mushroom) Stem Extract, Ethylhexylglycerin, Xanthan Gum, Hydroxypropyl Methylcellulose Stearoxy Ether, Adenosine, Butylene Glycol, Pyrus Communis (Pear) Fruit Extract, 1,2-Hexanediol, Rosa Damascena Flower Water, Allantoin, Caffeine, Acacia Senegal Flower/Stem Extract, Iris Florentina Root Extract, Cucumis Melo (melon) Fruit Extract, Hydrolyzed Collagen, Hydrogenated lecithin, Hedera Helix (Ivy) Leaf/Stem Extract, Cetearyl Alcohol, Stearic Acid, Centella Asiatica Extract, Ethyl Hexanediol, Hydrolyzed Elastin, Palmitoyl Tripeptide-5, Hydrolyzed Hyaluronic Acid, Hydrolyzed Sodium Hyaluronate, Dimethylsilanol Hyaluronate, Sodium Hyaluronate, Hyaluronic Acid, Hydrolyzed Collagen Extract, Potassium Hyaluronate, Sodium Hyaluronate Crosspolymer, Hydroxypropyltrimonium Hyaluronate, Ceramide NP, Sodium Hyaluronate Dimethylsilanol, Sodium Acetylated Hyaluronate, Cholesterol, Phytosphingosine, Ceramide NG, Ceramide NS, Ceramide AS, Ceramide AP, Collagen Extract, Ceramide EOP

OTHER SAFETY INFORMATION

Protect the product in the container from excessive heat and direct sun.

Sun alaert: Limiting sun exposure, wearing protective clothing, and using suncreens may reduce the risks of skin aging, skin cancer, and other harmful effects of the sun.